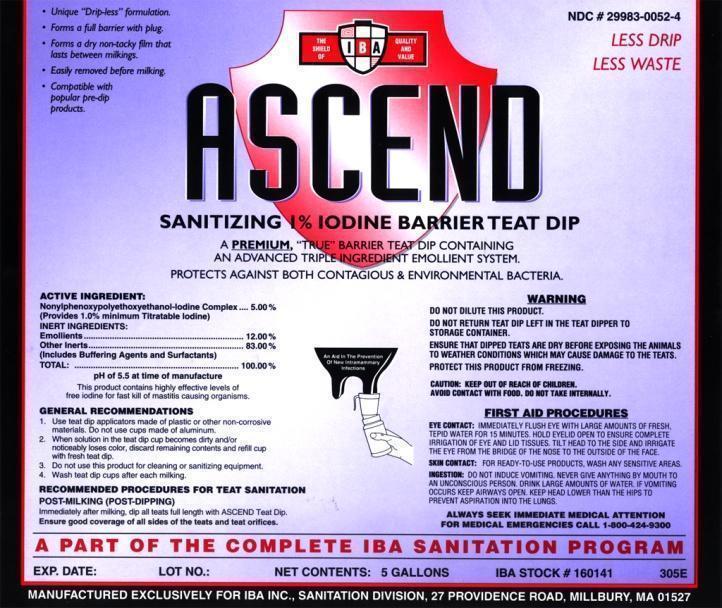 DRUG LABEL: ASCEND
NDC: 29983-0052 | Form: SOLUTION
Manufacturer: IBA
Category: animal | Type: OTC ANIMAL DRUG LABEL
Date: 20220719

ACTIVE INGREDIENTS: IODINE 10 g/1 L

Ascend Sanitizing 1% Iodine Barrier Teat Dip A PREMIUM, "TRUE" BARRIER TEAT DIP CONTAINING AN ADVANCED TRIPLE INGREDIENT EMOLLIENT SYSTEM. PROTECTS AGAINST BOTH CONTAGIOUS & ENVIRONMENTAL BACTERIA.

ACTIVE INGREDIENT

Nonylphenoxypolyethoxyethanol Iodine Complex.....5.00%
INERT INGREDIENTS
Emollients.......12.00%
Other Inerts.....83.00%
(Includes Buffering Agents and Surfactants)
Total.................100.00%
pH of 5.5 at time of manufacture
This product contains highly effective levels of free iodine for fast kill of mastitis causing organisms.

INDICATIONS AND USAGE

GENERAL RECOMMENDATIONS

1. Use teat dip applicators made of plastic or other non-corrosive materials. Do not use cups made of aluminum.
2. When solution in the teat dip cup becomes dirty and/or noticeably loses color, discard remaining contents and refill cup with fresh teat dip.
3. Do not use this product for cleaning or sanitizing equipment
4. Wash Teat Dip cups after each milking.
RECOMMENDED PROCEDURES FOR TEAT SANITATION
POST-MILKING (POST-DIPPING)
Immediately after milking dip all teats full length with ASCEND Teat Dip. Ensure good coverage of all sides of the teats and teat orifices.

A PART OF THE COMPLETE IBA SANITATION PROGRAM

WARNING

DO NOT DILUTE THIS PRODUCT
DO NOT RETURN TEAT DIP LEFT IN THE TEAT DIPPER TO STORAGE CONTAINER
ENSURE THAT DIPPED TEATS ARE DRY BEFORE EXPOSING THE ANIMALS TO WEATHER CONDITIONS WHICH MAY CAUSE DAMAGE TO THE TEATS.
PROTECT THIS PRODUCT FROM FREEZING.
CAUTION: KEEP OUT OF REACH OF CHILDREN.
AVOID CONTACT WITH FOOD. DO NOT TAKE INTERNALLY.

FIRST AID PROCEDURES

EYE CONTACT: IMMEDIATELY FLUSH EYE WITH LARGE
AMOUNTS OF FRESH, TEPID WATER FOR 15 MINUTES. HOLD EYELID OPEN TO
ENSURE COMPLETE IRRIGATION OF EYE AND LID TISSUES. TILT HEAD TO THE
SIDE AND IRRIGATE THE EYE FROM THE BRIDGE OF THE NOSE TO THE OUTSIDE OF
THE FACE.
SKIN CONTACT:FOR READY-TO-USE PRODUCTS, WASH ANY SENSITIVE AREAS.
INGESTION:DO NOT INDUCE VOMITING. NEVER GIVE ANYTHING BY MOUTH TO AN UNCONSCIOUS PERSON. DRINK LARGE AMOUNTS OF WATER. IF VOMITING OCCURS KEEP AIRWAYS
OPEN. KEEP HEAD LOWER THAN THE HIPS TO PREVENT ASPIRATION INTO THE
LUNGS.
ALWAYS SEEK IMMEDIATE MEDICAL ATTENTION

FOR MEDICAL EMERGENCIES CALL 1-800-424-9300